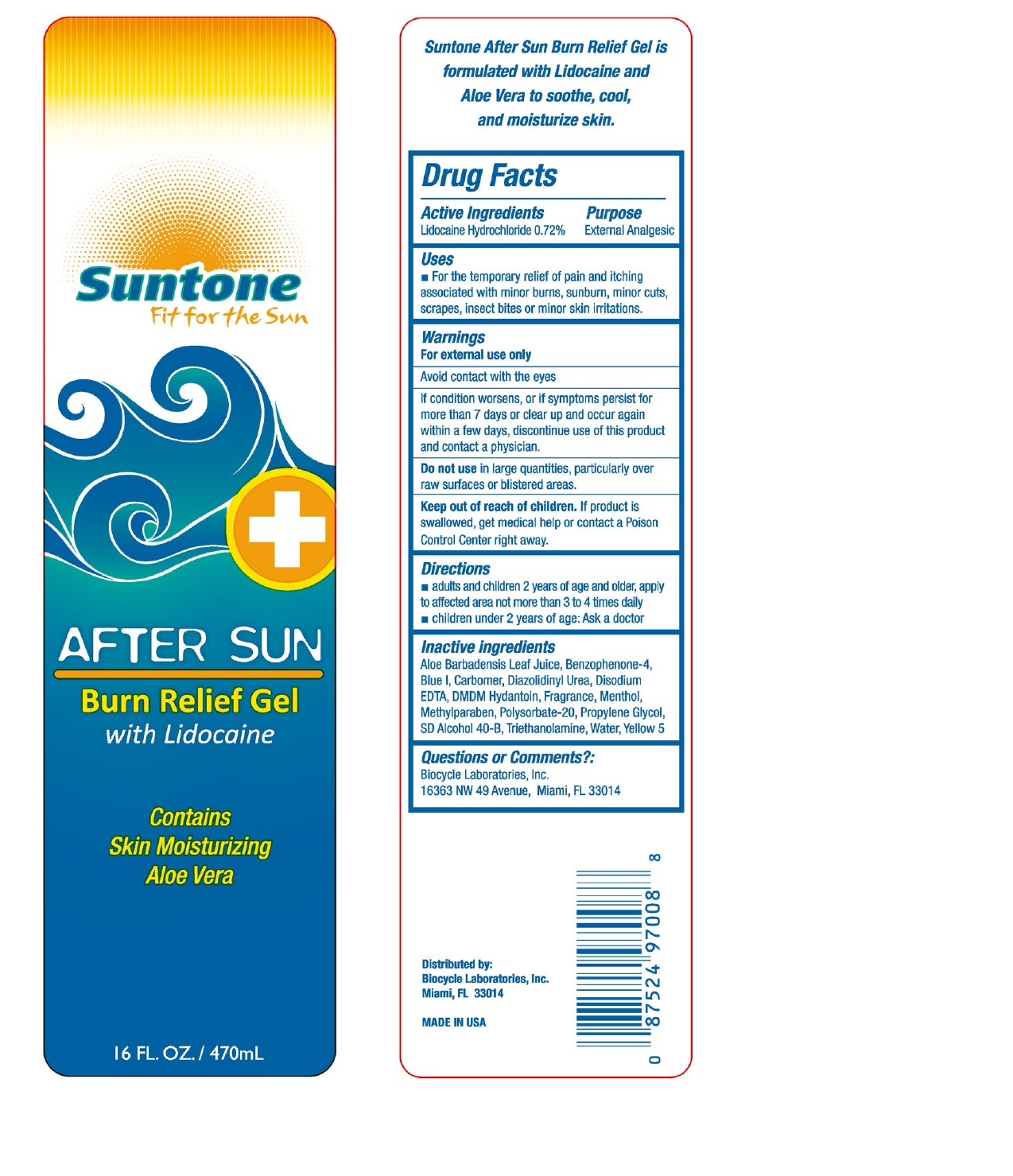 DRUG LABEL: Suntone
NDC: 58443-0125 | Form: GEL
Manufacturer: Prime Enterprises Inc.
Category: otc | Type: HUMAN OTC DRUG LABEL
Date: 20200608

ACTIVE INGREDIENTS: LIDOCAINE HYDROCHLORIDE 7.13 mg/1 mL
INACTIVE INGREDIENTS: ALOE VERA LEAF; SULISOBENZONE; DIAZOLIDINYL UREA; EDETATE DISODIUM; MENTHOL; METHYLPARABEN; TROLAMINE; CARBOMER 940; ALCOHOL; WATER; POLYSORBATE 20; PROPYLENE GLYCOL; DMDM HYDANTOIN

Suntone After Sun Burn Relief Gel with Lidocaine

Active Ingredients

Lidocaine Hydrochloride (0.72%)

Purpose

External Analgesic

Uses

For the temporary relief of pain and itching associated with minor burns, sunburn, minor cuts, scrapes, insect bites or minor skin irritations.

WARNINGS

For external use only.

Avoid contact with the eyes.

If condition worsens, or if symptoms persist for more than 7 days or clear up and occur again within a few days, discontinue use of this product and contact a physician.

Do not use in large quantities, particularly over raw surfaces or blistered areas.

Keep out of reach of children. If product is swallowed, get medical help or contact a Poison Control Center right away..

Directions

- Adults and children 2 years of age and older, apply to affected area not more than 3 to 4 times daily.
- Children under 2 years of age: Ask a doctor

INACTIVE INGREDIENT

Aloe Barbadensis Leaf Juice, Benzophenone-4, Blue 1, Carbomer, Diazolidinyl Urea, Disodium EDTA, DMDM Hydantoin, Fragrance, Menthol, Methylparaben, Polysorbate 20, Propylene Glycol, SD Alcohol 40-B, Triethanolamine, Water, Yellow 5

Questions or Comments?

Biocycle Laboratories, Inc.

16363 NW 49 Avenue, Miami, FL 33014